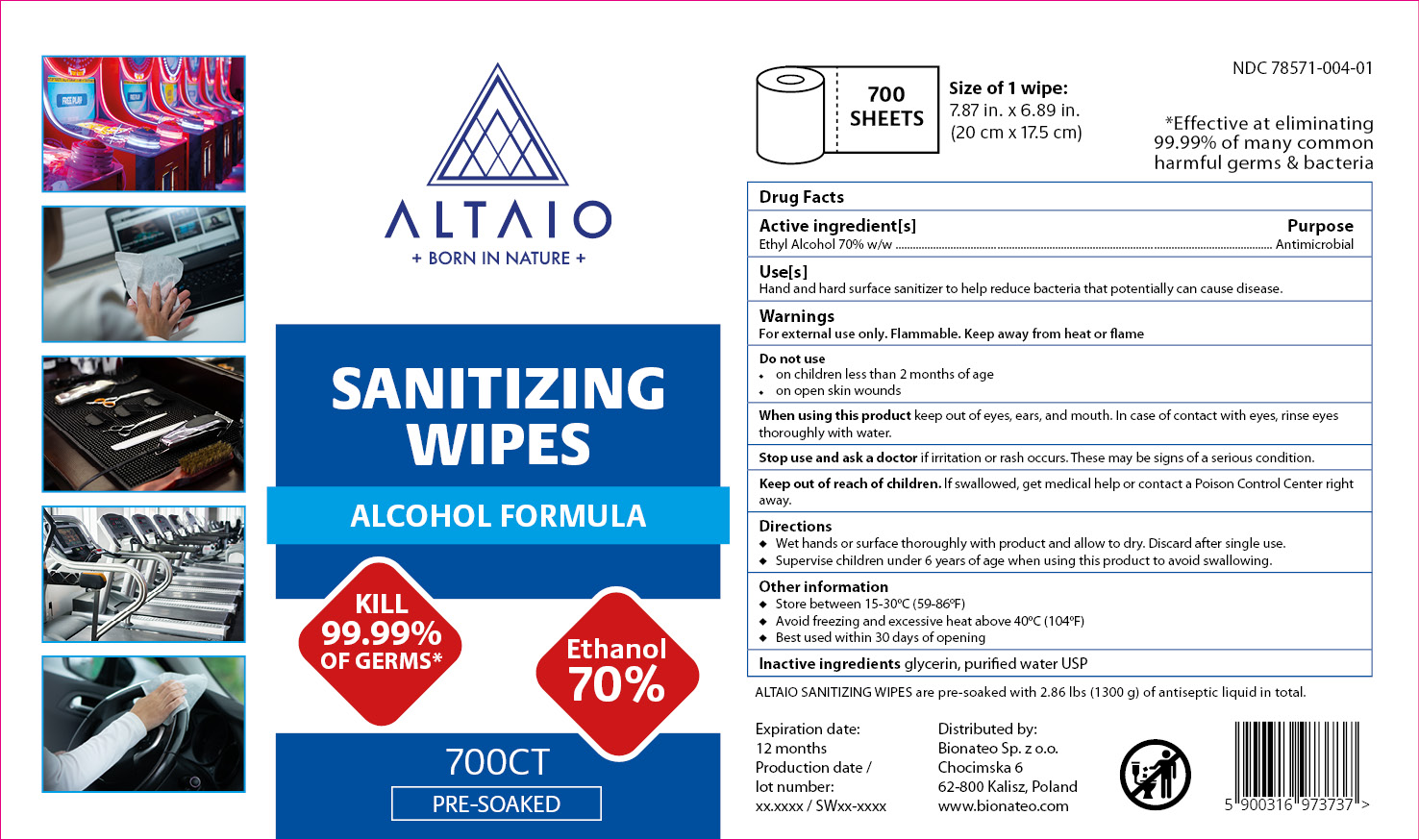 DRUG LABEL: ALTAIO Sanitizing Wipes
NDC: 78571-004 | Form: CLOTH
Manufacturer: BIONATEO SP Z O O
Category: otc | Type: HUMAN OTC DRUG LABEL
Date: 20200622

ACTIVE INGREDIENTS: ALCOHOL 70 g/100 g
INACTIVE INGREDIENTS: GLYCERIN 3 g/100 g; WATER

The ALTAIO Sanitizing Wipes is a product manufactured using only the following United States Pharmacopoeia (USP) grade ingredients in the preparation of the product:

1. Alcohol (ethanol) (USP or Food Chemical Codex (FCC) grade) (70%, volume/volume (w/w)) in an aqueous solution denatured according to Alcohol and Tobacco Tax and Trade Bureau regulations in 27 CFR part 20.
2. Glycerin (3% w/w).
3. Sterile distilled water or boiled cold water.

The firm does not add other active or inactive ingredients. Different or additional ingredients may impact the quality and potency of the product.

Active Ingredient(s)

Ethyl Alcohol 70% w/w. Purpose: Antimicrobial

Purpose

Antimicrobial, Hand Sanitizer, Hard Surface Sanitizer

Use

Hand and hard surface sanitizer to help reduce bacteria that potentially can cause disease.

Warnings

For external use only. Flammable. Keep away from heat or flame

Do not use

- on children less than 2 months of age
- on open skin wounds

When using this product keep out of eyes, ears, and mouth. In case of contact with eyes, rinse eyes thoroughly with water.
Stop use and ask a doctor if irritation or rash occurs. These may be signs of a serious condition.
Keep out of reach of children. If swallowed, get medical help or contact a Poison Control Center right away.

Stop use and ask a doctor if irritation or rash occurs. These may be signs of a serious condition.

Keep out of reach of children. If swallowed, get medical help or contact a Poison Control Center right away.

Directions

- Wet hands or hard surface thoroughly with product and allow to dry. Discard after single use.
- Supervise children under 6 years of age when using this product to avoid swallowing.

Other information

- Store between 15-30oC (59-86oF)
- Avoid freezing and excessive heat above 40oC (104oF)
- Best used within 30 days of opening

Inactive ingredients

glycerin, purified water USP

Package Label - Principal Display Panel

ALTAIO Sanitizing Wipes 700CT NDC: 78571-004-01